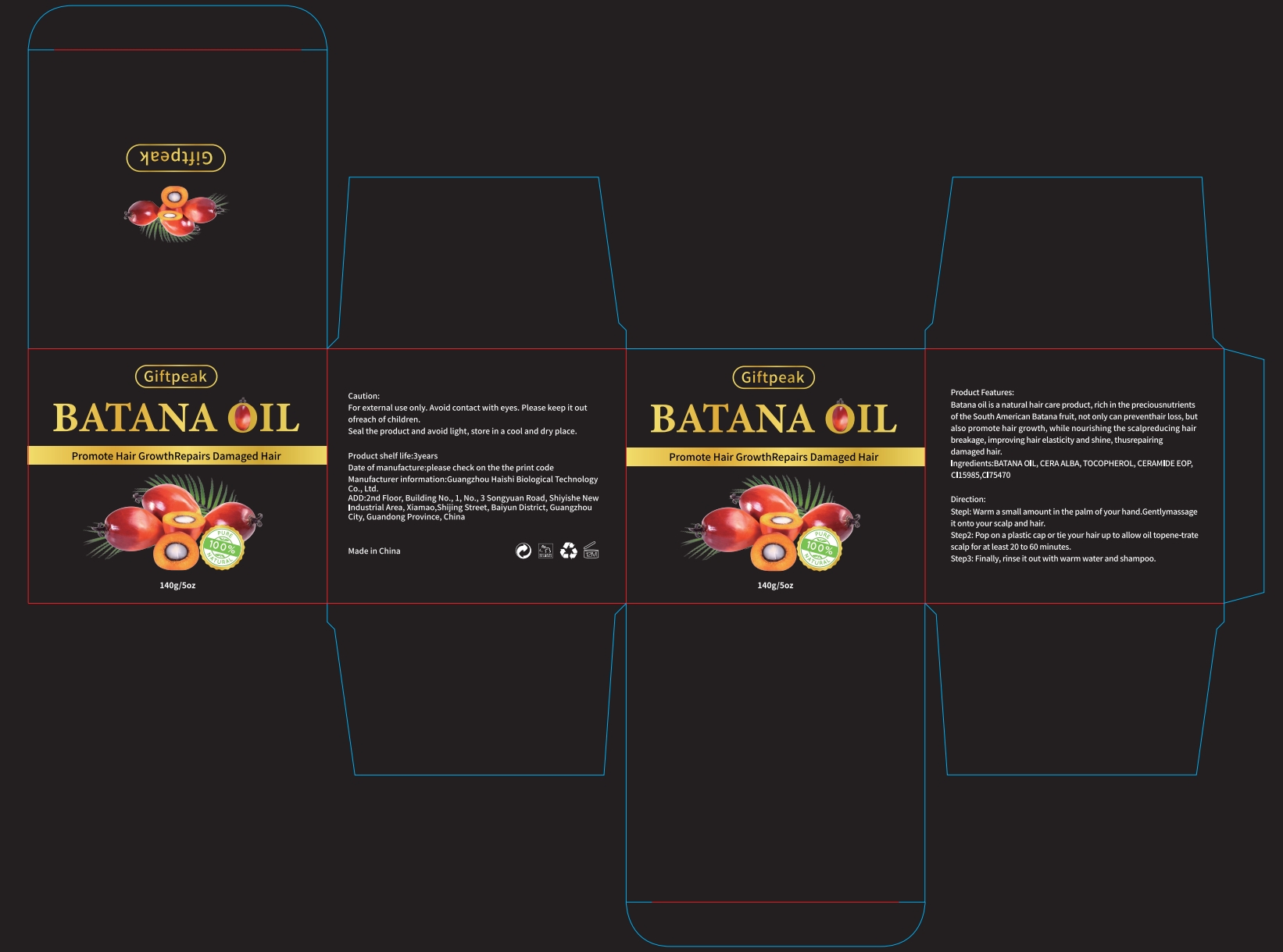 DRUG LABEL: Guangzhou Yilong Cosmetics Co., Ltd
NDC: 74458-003 | Form: CREAM
Manufacturer: Guangzhou Yilong Cosmetics Co., Ltd
Category: otc | Type: HUMAN OTC DRUG LABEL
Date: 20241001

ACTIVE INGREDIENTS: TOCOPHEROL 1 g/99 g
INACTIVE INGREDIENTS: 1,3-BIS(BENZOTHIAZOL-2-YLTHIOMETHYL)UREA

Active Ingredient

TOCOPHEROL, CERAMIDE EOP

Purpose

Batana oil is a natural hair care product,
rich in the preciousnutrientsofthe South American Batana fruit,
not only can preventhair loss, butalso promote hair growth,
while nourishing the scalpreducing hairbreakage,
improvinghair elasticity and shine, thusrepairingdamaged hair.

Directions

Stepl: Warm a small amount in the palm ofyour hand.Gentlymassageit onto your scalp and hair.
Step2: Pop on a plastic cap or tie your hair up to allow oil topene-tratescalp for at least 20 to 60 minutes.
Step3: Finally, rinse it out with warm water and shampoo.

Warnings

For external use only

Do not use on damaged or broken skin.

When Using

When using this productkeep out of ees.Ringe with wate to remove.

Stop Use

Stop use and ask doctor if rash occurs.

Keep Out Of Reach Of Children

Inactive ingredients

BATANA OIL, CERA ALBA, C115985,C175470

DOSAGE AND ADMINISTRATION

Warm a small amount in the palm ofyour hand.Gentlymassageit onto your scalp and hair